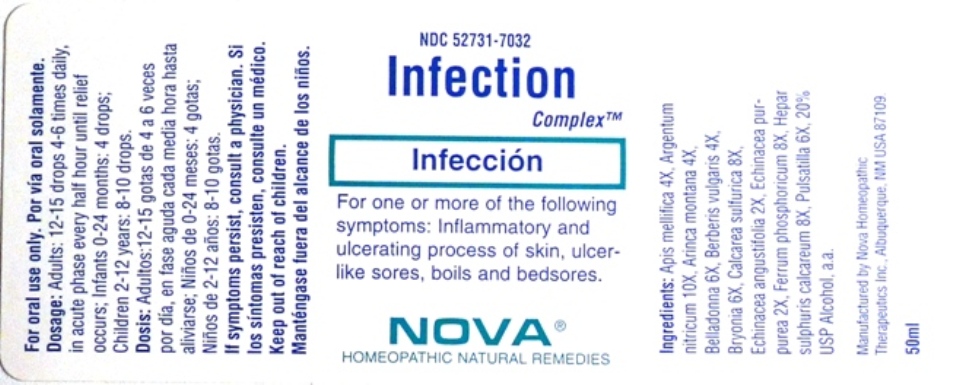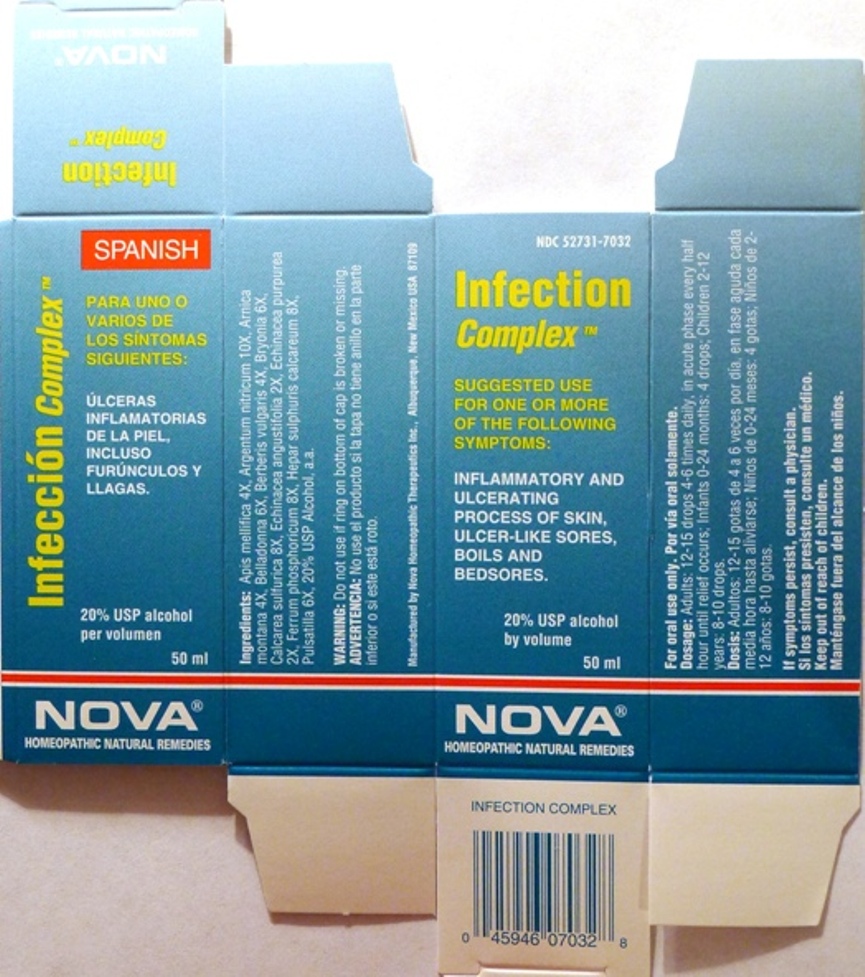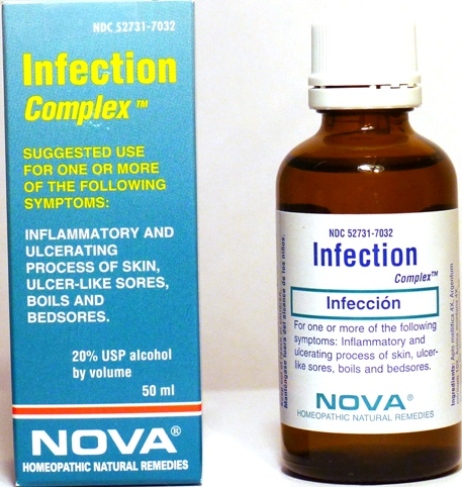 DRUG LABEL: Infection Complex
NDC: 52731-7032 | Form: LIQUID
Manufacturer: Nova Homeopathic Therapeutics, Inc.
Category: homeopathic | Type: HUMAN OTC DRUG LABEL
Date: 20110601

ACTIVE INGREDIENTS: APIS MELLIFERA 4 [hp_X]/1 mL; SILVER CATION 10 [hp_X]/1 mL; ARNICA MONTANA 4 [hp_X]/1 mL; ATROPA BELLADONNA 6 [hp_X]/1 mL; BERBERIS VULGARIS ROOT BARK 4 [hp_X]/1 mL; BRYONIA ALBA ROOT 6 [hp_X]/1 mL; CALCIUM CATION 8 [hp_X]/1 mL; ECHINACEA ANGUSTIFOLIA 2 [hp_X]/1 mL; ECHINACEA PURPUREA 2 [hp_X]/1 mL; FERRUM PHOSPHORICUM 8 [hp_X]/1 mL; CALCIUM CATION 8 [hp_X]/1 mL; PULSATILLA VULGARIS 6 [hp_X]/1 mL
INACTIVE INGREDIENTS: ALCOHOL

Infection Complex

Purpose:

Suggested use for one or more of the following symptoms:

Inflammatory and ulcerating process of skin, ulcer-like sores, boils and bedsores.

Usage and Dosage:

For oral use only.

DOSAGE AND ADMINISTRATION

Adults:
In Acute Phase:
12-15 drops, every half hour until relief occurs
When Relief Occurs:
12-15 drops, 4-6 times per day
Children 2-12 years:
8-10 drops, 4-6 times per day

Infants 0-24 months:
4 drops, 4-6 times per day

Warnings:

Keep out of reach of children.

WARNINGS

If symptoms persist, consult a physician.
Do not use if ring on bottom of cap is broken or missing.

Active Ingredients:

Apis mellifica 4X, Argentum Nitricum 10X, Arnica montana 4X, Belladonna 6X, Berberis vulgaris 4X, Bryonia 6X, Calcarea sulfurica 8X, Echinacea angustifolia 2X, Echinacea purpurea 2X, Ferrum phosphoricum 8X, Hepar sulphuris calcareum 8X, Pulsatilla 6X

Inactive Ingredients:

Alcohol, 20% USP

QUESTIONS

Manufactured by Nova Homeopathic Therapeutics Inc., Albuquerque, New Mexico USA 87109
1-800-225-8094

PACKAGE LABEL

Infection Complex Product

Infection Complex Bottle Label

Infection Complex Box